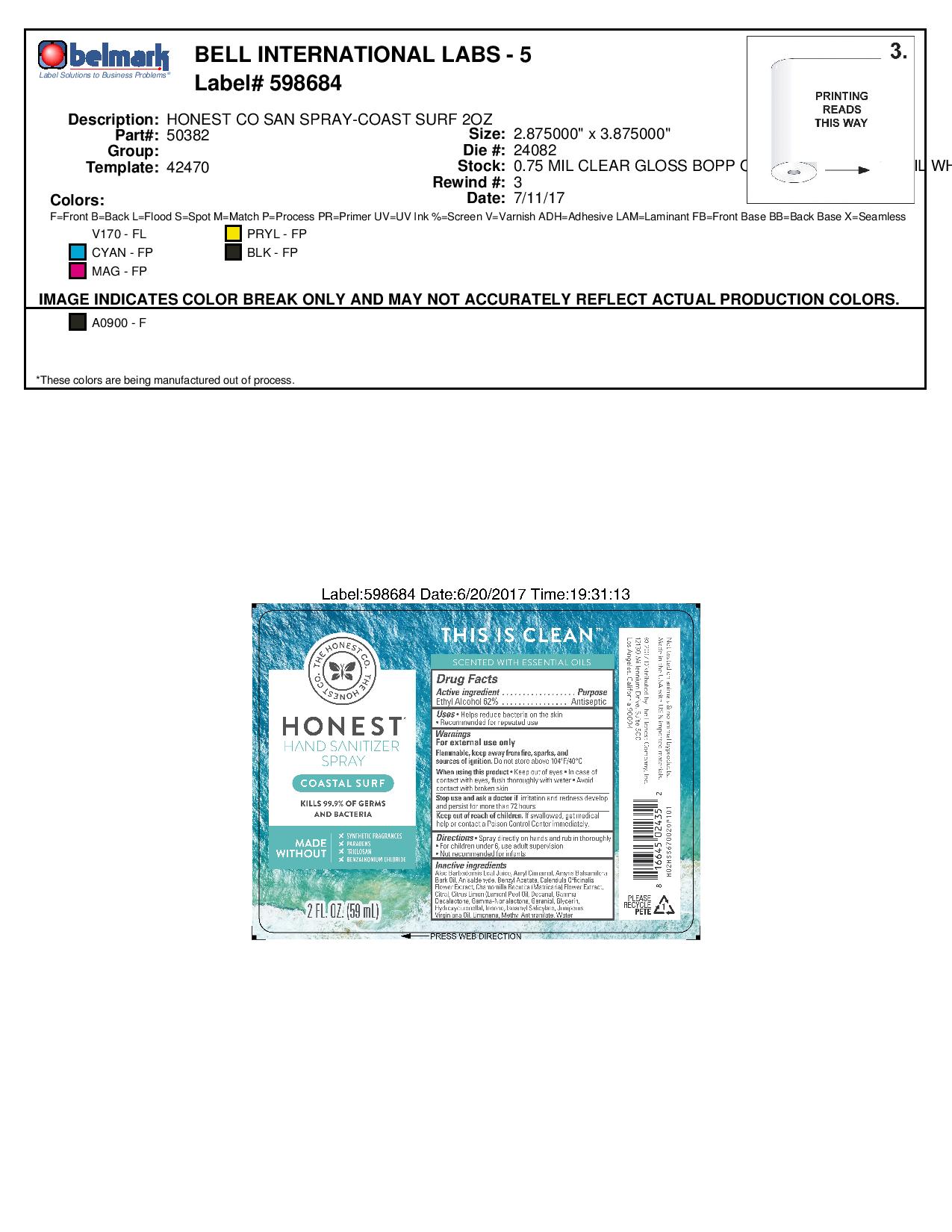 DRUG LABEL: Hand Sanitizer
NDC: 69366-310 | Form: SPRAY
Manufacturer: The Honest Company
Category: otc | Type: HUMAN OTC DRUG LABEL
Date: 20241219

ACTIVE INGREDIENTS: ALCOHOL 62 mL/100 mL
INACTIVE INGREDIENTS: CITRAL; GERANIOL; IONONE; JUNIPERUS VIRGINIANA OIL; METHYL ANTHRANILATE; CHAMOMILE; GLYCERIN; .ALPHA.-AMYLCINNAMALDEHYDE; BENZYL ACETATE; P-ANISALDEHYDE; LEMON OIL; DECANAL; WATER; CALENDULA OFFICINALIS FLOWER; ALOE VERA LEAF; AMYRIS BALSAMIFERA OIL; .GAMMA.-NONALACTONE; ISOAMYL SALICYLATE; LIMONENE, (+)-; .GAMMA.-DECALACTONE; HYDROXYCITRONELLAL

Honest Company Hand Sanitizer Spray Coastal Surf 2 oz bottle

Active ingredient

Ethyl Alcohol 62%

Purpose

Antiseptic

Uses

Helps reduce bacteria on the skin

recommended for repeated use

Warnings

For external use only

Flammable, keep away from fire, sparks, and sources of ignition. Do not store above 104 oF/40 oC

When using this product keep out of eyes. In case of contact with eyes, flush thoroughly with water. Avoid contact with broken skin.

Stop use and ask a doctor if irritation and redness develop and persist for more than 72 hours.

Keep out of reach of children. If swallowed, get medical help or contact a Poison Control Center immediately.

Directions

Spray directly on hands and rub un thoroughly

For children under 6, use adult supervision

Not recommended for infants

Inactive Ingredients

Aloe Barbadensis Leaf Juice, Amyl Cinnamal, Amyris Balsamifera Bark Oil, Anisaldehyde, Benzyl Acetate, Calendula Officinalis Flower Extract, Chamomilla Recutita (Matricaria) Flower Extract, Citral, Citrus Limon (Lemon) Peel Oil, Decanol, Gamma-Decalactone, Gamma-Nonalactone, Geraniol, Glycerin, Hydroxycitronellal, Ionone, Isoamyl Salicylate, Juniperus Virginiana Oil, Limonene, Methyl Anthranilate, Water